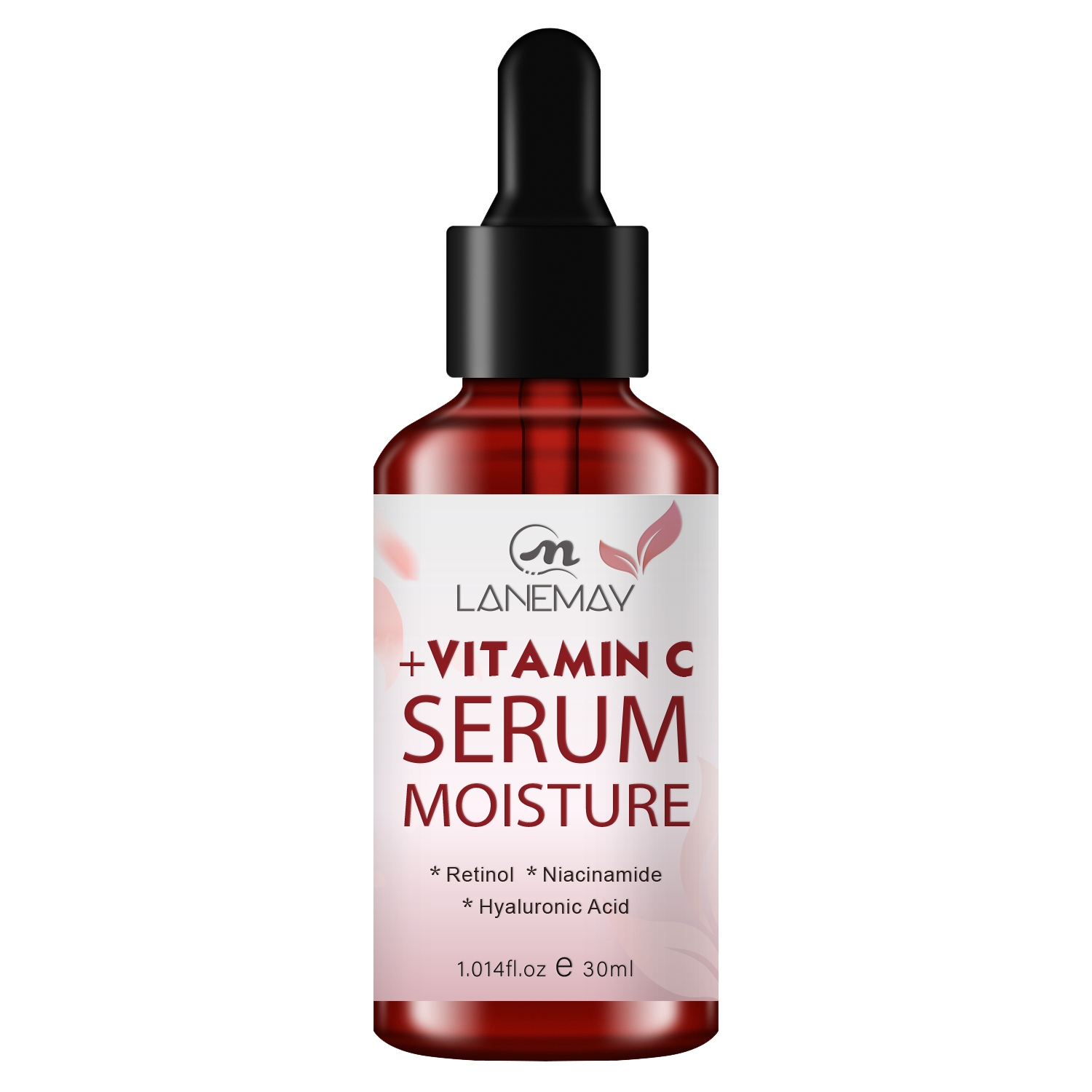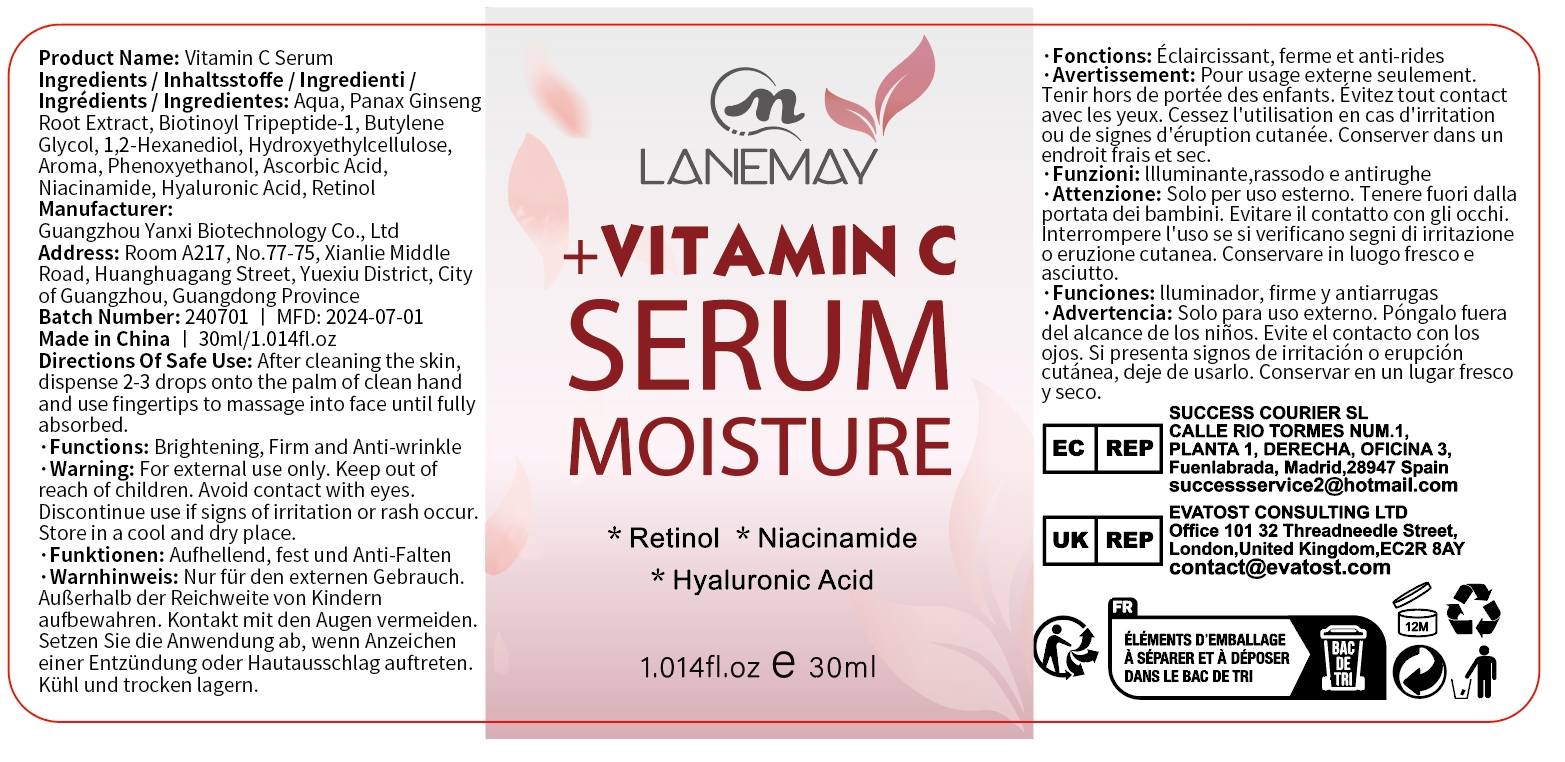 DRUG LABEL: Vitamin C Serum
NDC: 84025-189 | Form: LIQUID
Manufacturer: Guangzhou Yanxi Biotechnology Co.. Ltd
Category: otc | Type: HUMAN OTC DRUG LABEL
Date: 20240919

ACTIVE INGREDIENTS: PHENOXYETHANOL 5 mg/30 mL; ASCORBIC ACID 3 mg/30 mL
INACTIVE INGREDIENTS: WATER

DOSAGE AND ADMINISTRATION

Serum for firming skin and reducing wrinkles

WARNINGS

keep out of children

INACTIVE INGREDIENT

AQUA

INDICATIONS AND USAGE

For daily skin care

Keep out of children

PURPOSE

Moisturizes the skin and delays skin aging